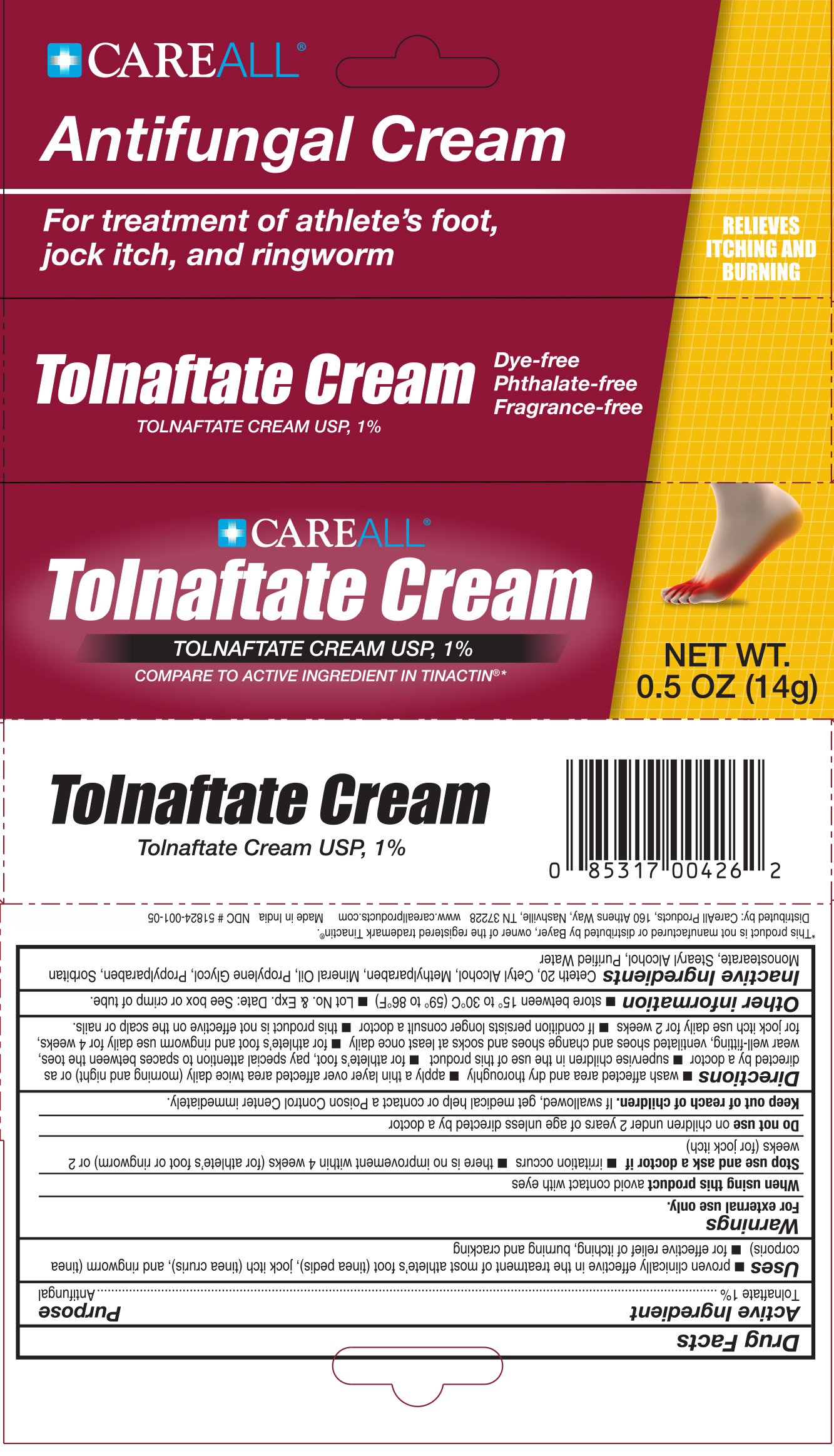 DRUG LABEL: CAREALL Tolnaftate
NDC: 51824-001 | Form: CREAM
Manufacturer: New World Imports, Inc
Category: otc | Type: HUMAN OTC DRUG LABEL
Date: 20251201

ACTIVE INGREDIENTS: TOLNAFTATE 10 mg/1 g
INACTIVE INGREDIENTS: PROPYLENE GLYCOL; MINERAL OIL; STEARYL ALCOHOL; CETYL ALCOHOL; SORBITAN MONOSTEARATE; CETETH-20; WATER; METHYLPARABEN; PROPYLPARABEN

Drug Facts

ACTIVE INGREDIENT

Tolnaftate 1%

PURPOSE

Antifungal

Keep out of reach of children. If Swallowed, get medical help or contact a Poison Control center right away.

INDICATIONS AND USAGE

- Proven clinically effective in the treatment of athlete's foot (tinea pedis), jock itch (tinea cruris), ringworm (tinea corporis)
- For effective relief of itching, burning and cracking

WARNINGS

For external use only

When using this productavoid contact with the eyes

Stop use and ask a doctor if

- irritation occurs
- there is no improvement within 4 weeks (for athlete's foot or ring worm) or 2 weeks (for jock itch).

Do not useon children under 2 years of age unless directed by a doctor

DOSAGE AND ADMINISTRATION

- Wash affected area and dry thoroughly
- Apply a thin layer over affected area twice daily (morning and night) or as directed by a doctor
- Supervise children in the use of this product
- for athlete's foot, pay special attention to spaces between the toes, wear well-fitting, ventilated shows and change shoes and socks at least once daily
- For athlete's foot and ringworm use daily for 4 weeks, for jock itch use daily for 2 weeks.
- If condition persists longer consult a doctor
- This product is not effective on scalp or nails

INACTIVE INGREDIENT

Ceteth 20, Cetyl Alcohol, Methylparaben, Mineral Oil, Propylene Glycol, Propylparaben, Sorbitan Monostearate, Steryl Alcohol, Purified Water